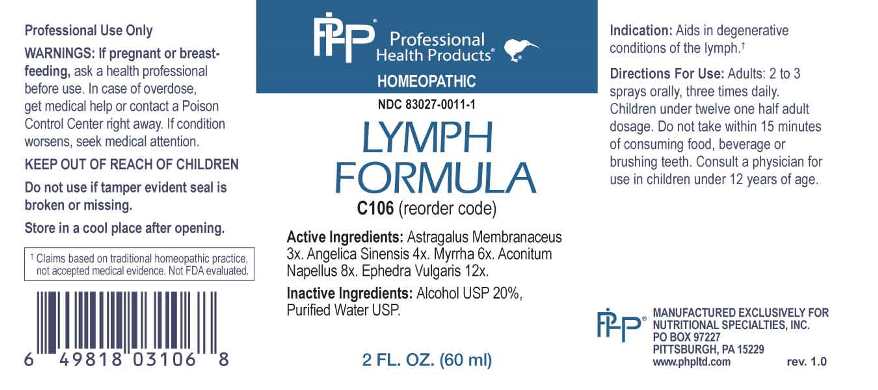 DRUG LABEL: Lymph Formula
NDC: 83027-0011 | Form: SPRAY
Manufacturer: Nutritional Specialties, Inc.
Category: homeopathic | Type: HUMAN OTC DRUG LABEL
Date: 20240311

ACTIVE INGREDIENTS: ASTRAGALUS MONGHOLICUS ROOT 3 [hp_X]/1 mL; ANGELICA SINENSIS ROOT 4 [hp_X]/1 mL; MYRRH 6 [hp_X]/1 mL; ACONITUM NAPELLUS WHOLE 8 [hp_X]/1 mL; EPHEDRA DISTACHYA FLOWERING TWIG 12 [hp_X]/1 mL
INACTIVE INGREDIENTS: WATER; ALCOHOL

DRUG FACTS:

ACTIVE INGREDIENTS:

Astragalus Membranaceus 3X, Angelica Sinensis 4X, Myrrha 6X, Aconitum Napellus 8X, Ephedra Vulgaris 12X.

PURPOSE:

Aids in degenerative conditions of the lymph.†

†Claims based on traditional homeopathic practice, not accepted medical evidence. Not FDA evaluated.

WARNINGS:

Professional Use Only

If pregnant or breast-feeding, ask a health professional before use.

In case of overdose, get medical help or contact a Poison Control Center right away.

If condition worsens, seek medical attention.

KEEP OUT OF REACH OF CHILDREN

Do not use if tamper evident seal is broken or missing.

Store in a cool place after opening

KEEP OUT OF REACH OF CHILDREN:

In case of overdose, get medical help or contact a Poison Control Center right away.

DIRECTIONS:

Adults: 2 to 3 sprays orally, three times daily. Children under twelve one half adult dosage. Do not take within 15 minutes of consuming food, beverage or brushing teeth. Consult a physician for use in children under 12 years of age.

INDICATIONS:

Aids in degenerative conditions of the lymph.†

†Claims based on traditional homeopathic practice, not accepted medical evidence. Not FDA evaluated.

INACTIVE INGREDIENTS:

Alcohol USP 20%, Purified Water USP.

QUESTIONS:

MANUFACTURED EXCLUSIVELY FOR

NUTRITIONAL SPECIALTIES, INC.

PO BOX 97227

PITTSBURG, PA 15229

www.phpltd.com

PACKAGE LABEL DISPLAY:

Professional

Health Products

HOMEOPATHIC

NDC 83027-0011-1

LYMPH FORMULA

2 FL. OZ (60 ml)